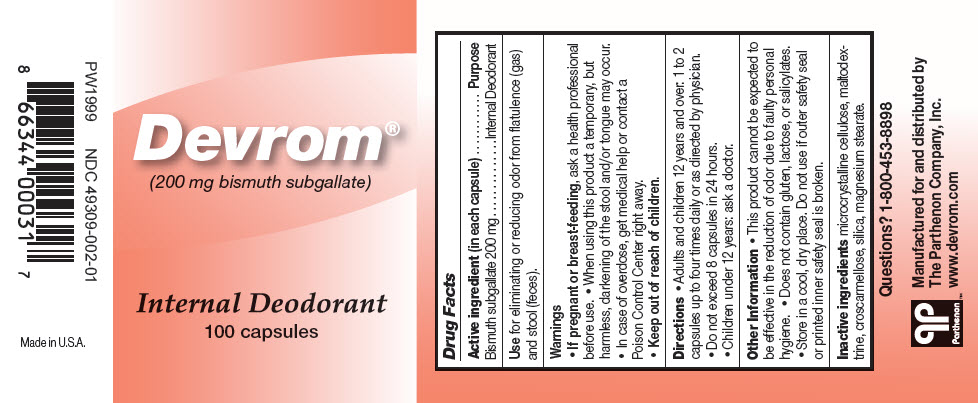 DRUG LABEL: Devrom
NDC: 49309-002 | Form: CAPSULE
Manufacturer: The Parthenon Co., Inc.
Category: otc | Type: HUMAN OTC DRUG LABEL
Date: 20241112

ACTIVE INGREDIENTS: BISMUTH SUBGALLATE 200 mg/1 1
INACTIVE INGREDIENTS: MAGNESIUM STEARATE; MICROCRYSTALLINE CELLULOSE; MALTODEXTRIN; CROSCARMELLOSE SODIUM; SILICON DIOXIDE

Devrom®

Drug Facts

Active ingredient (in each capsule)

Bismuth subgallate 200 mg

Purpose

Internal Deodorant

INDICATIONS AND USAGE

Use for eliminating or reducing odor from flatulence (gas) and stool (feces).

Warnings

PREGNANCY OR BREAST FEEDING

- If pregnant or breast-feeding, ask a health professional before use.
- When using this product a temporary, but harmless, darkening of the stool and/or tongue may occur.
- In case of overdose, get medical help or contact a Poison Control Center right away.

- Keep out of reach of children.

Directions

- Adults and children 12 years and over: 1 to 2 capsules up to four times daily or as directed by physician.
- Do not exceed 8 capsules in 24 hours.
- Children under 12 years: ask a doctor.

Other Information

- This product cannot be expected to be effective in the reduction of odor due to faulty personal hygiene.
- Does not contain gluten, lactose, or salicylates.
- Store in a cool, dry place. Do not use if outer safety seal or printed inner safety seal is broken.

Inactive ingredients

microcrystalline cellulose, maltodextrine, croscarmellose, silica, magnesium stearate.

Questions?

1-800-453-8898

Manufactured for and distributed by
The Parthenon Company, Inc.

PRINCIPAL DISPLAY PANEL - 200 mg Capsule Bottle Label

Devrom®
(200 mg bismuth subgallate)

Internal Deodorant
100 capsules